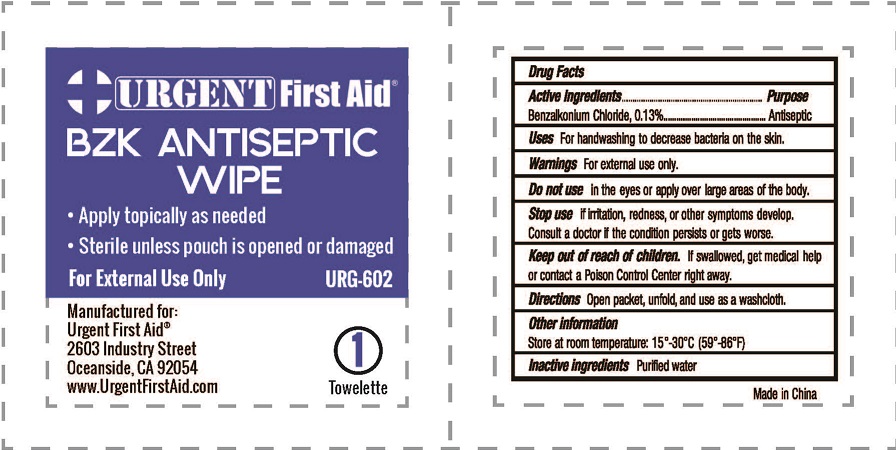 DRUG LABEL: Antiseptic Wipe
NDC: 71310-007 | Form: CLOTH
Manufacturer: Taizhou Kangping Medical Science And Technology Co., Ltd.
Category: otc | Type: HUMAN OTC DRUG LABEL
Date: 20230226

ACTIVE INGREDIENTS: BENZALKONIUM CHLORIDE 1.3 mg/1 mL
INACTIVE INGREDIENTS: WATER

Urgent First Aid
BZK ANTISEPTIC WIPE

Active ingredients

Benzalkonium Chloride, 0.13%

Purpose

Antiseptic

Uses

For handwashing to decrease bacteria on the skin.

Warnings

For external use only.

Do not use

in the eyes or apply over large areas of the body.

Stop use

if irritation, redness or other symptoms develop.

Consult a doctor if the condition persists or gets worse.

Keep out of reach of children.

If swallowed, get medical help or contact a Poison Control Center right away.

Directions

Open packet, unfold and use as a washcloth.

Other information

Store at room temperature: 15°-30°C (59°-86°F)

Inactive ingredients

Purified water

BZK ANTISEPTIC WIPE

• Apply topically as needed

• Sterile unless pouch is opened or damaged

For External Use Only